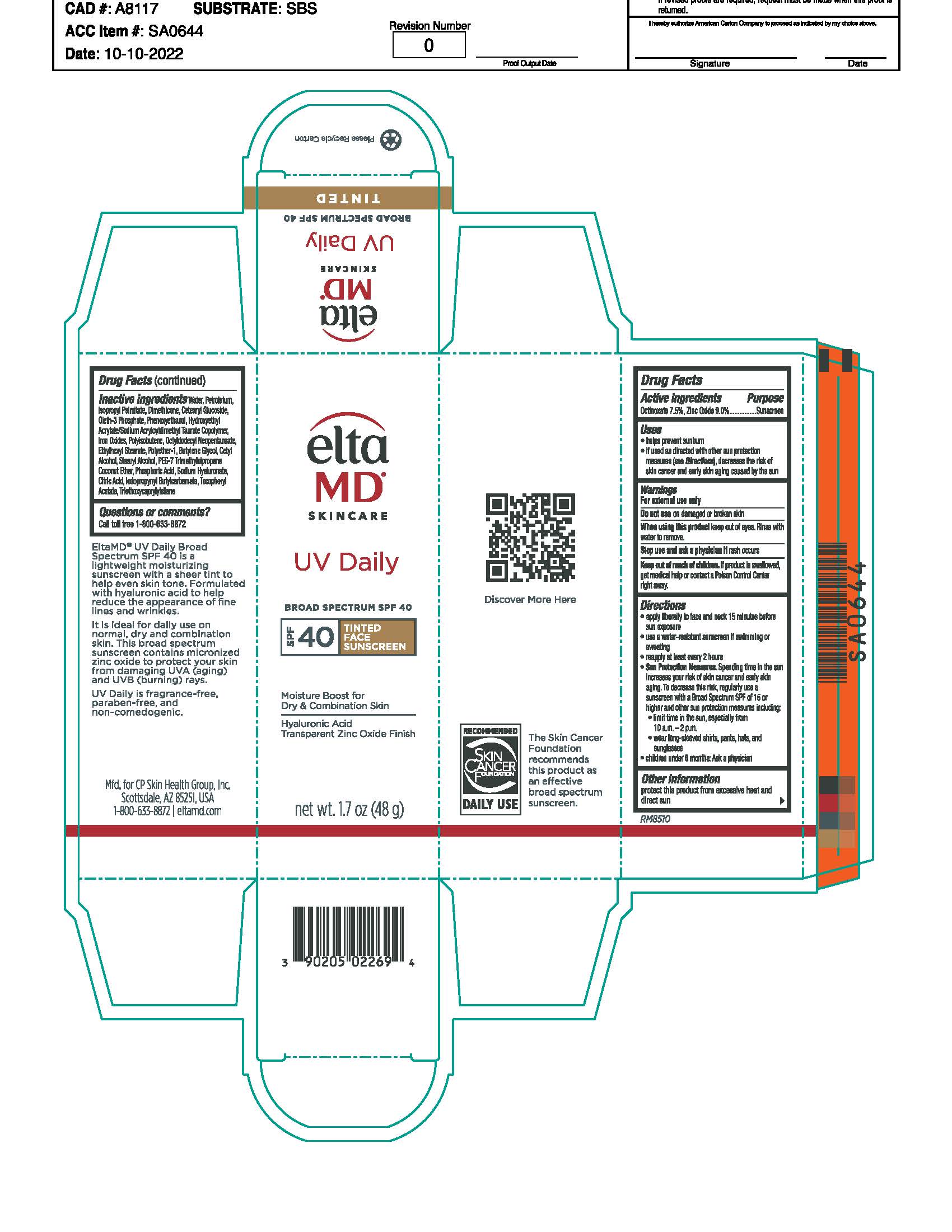 DRUG LABEL: EltaMD UV Daily Tinted SPF40
NDC: 72043-2269 | Form: LOTION
Manufacturer: CP Skin Health Group, Inc.
Category: otc | Type: HUMAN OTC DRUG LABEL
Date: 20231109

ACTIVE INGREDIENTS: ZINC OXIDE 90 g/1000 g; OCTINOXATE 75 g/1000 g
INACTIVE INGREDIENTS: WATER; PHENOXYETHANOL; CETEARYL GLUCOSIDE; ISOPROPYL PALMITATE; OCTYL STEARATE; OCTYLDODECYL NEOPENTANOATE; OLETH-3 PHOSPHATE; FERRIC OXIDE RED; FERRIC OXIDE YELLOW; FERROSOFERRIC OXIDE; DIMETHICONE; PETROLATUM; TRIETHOXYCAPRYLYLSILANE; CITRIC ACID MONOHYDRATE; .ALPHA.-TOCOPHEROL ACETATE, DL-; HYALURONATE SODIUM; HYDROXYETHYL ACRYLATE/SODIUM ACRYLOYLDIMETHYL TAURATE COPOLYMER (100000 MPA.S AT 1.5%); POLYISOBUTYLENE (1000 MW)

EltaMD UV Daily Tinted SPF40

Warnings

For external use only Do not use on damaged or broken skin When using this product keep out of eyes. Rinse with water to remove. Stop use and ask physician if rash occurs Keep out of reach of children. If product is swallowed, get medical help or contact a Poison Control Center right away.

Active Ingredients

Zinc Oxide 9.0% Sunscreen

Octinoxate 7.5% Sunscreen

Uses

Helps prevent sunburn If used as directed with other sun protection measures (see Directions), decreases the risk of skin cancer and early skin aging caused by the sun.

Uses

Helps prevent sunburn If used as directed with other sun protection measures (see Directions), decreases the risk of skin cancer and early skin aging caused by the sun.

Directions

Apply liberally to face, neck and backs of hands 15 minutes before sun exposure Use a water-resistant sunscreen if swimming or sweating Reapply at least every 2 hours Sun Protection Measures. Spending time in the sun increases your risk of skin cancer and early skin aging. To decrease this risk, regularly use a sunscreen with a broad-spectrum SPF of 15 or higher and other sun protection measures including: limit time in the sun, especially from 10 a.m. - 2 p.m. wear long-sleeve shirts, pants, hats and sunglasses children under 6 months: Ask a physician

Inactive Ingredients

purified water, petrolatum, isopropyl palmitate, cetearyl glucoside, dimethicone hydroxyethyl acrylate/sodium acryloyldimethyl taurate copolymer, polyisobutene, PEG-7 trimethylolpropane coconut ether, sodium hyaluronate, tocopheryl acetate, polyether-1, citric acid, oleth-3 phosphate, phenoxyethanol, butylene glycol, idodpropynyl butylcarbamate, triethoxycaprylylsilane, iron oxides, ethylhexyl stearate, octyldodecyl neopentanoate

KEEP OUT OF REACH OF CHILDREN